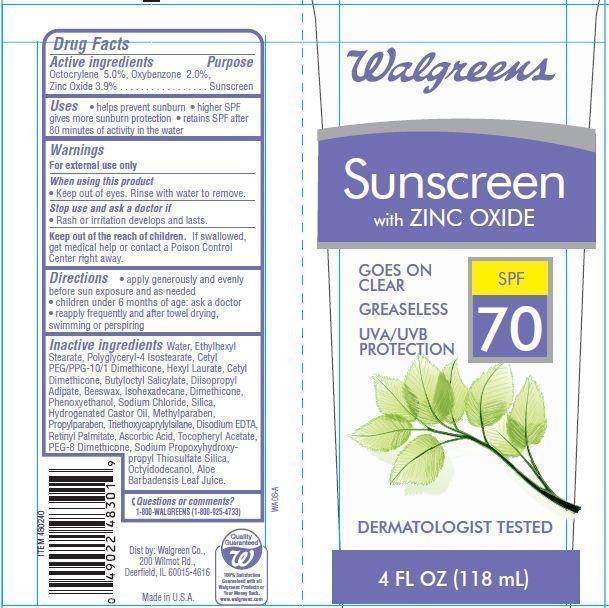 DRUG LABEL: Walgreens SunscreenSPF 70
          
NDC: 0363-4009 | Form: LOTION
Manufacturer: WALGREEN CO.
Category: otc | Type: HUMAN OTC DRUG LABEL
Date: 20121204

ACTIVE INGREDIENTS: OCTOCRYLENE 5 g/100 g; OXYBENZONE 2 g/100 g; ZINC OXIDE 3.9 g/100 g
INACTIVE INGREDIENTS: WATER; ETHYLHEXYL STEARATE; POLYGLYCERYL-4 ISOSTEARATE; HEXYL LAURATE; BUTYLOCTYL SALICYLATE; DIISOPROPYL ADIPATE; YELLOW WAX; ISOHEXADECANE; DIMETHICONE; PHENOXYETHANOL; SODIUM CHLORIDE; SILICON DIOXIDE; HYDROGENATED CASTOR OIL; METHYLPARABEN; PROPYLPARABEN; EDETATE DISODIUM; VITAMIN A PALMITATE; ASCORBIC ACID; .ALPHA.-TOCOPHEROL ACETATE; OCTYLDODECANOL; ALOE VERA LEAF

Drug Facts

Active ingredients

Octocrylene 5.0%
Oxybenzone 2.0%
Zinc Oxide 3.9%
Purpose
Sunscreen

Warnings

For external use only

When using this product

- Keep out of eyes. Rinse with water to remove.

stop use and ask a doctor if

- rash or irritation develops and lasts

keep out of reach of children.

If swallowed get medical help or contact a Poison Control Center right away.

Directions

- apply generously and evenly before sun exposure and as needed
- children under 6 months of age:ask a doctor
- reapply frequently and after towel drying, swimming or perspiring

Questions or comments?

1-800-WALGREENS(1-800-925-4733)

Inactive Ingredients

Water, Ethylhexyl Stearate, Cetyl Dimethicone, Butyloctyl Salicylate, Diisopropyl Adipate, Polyglyceryl-4 Isostearate, Cetyl PEG/PPG-10/1 Dimethicone, Hexyl Laurate, Beeswax, Isohexadecane, Sodium Chloride, Silica, Hydrogenated Castor Oil, Dimethicone, Triethoxycaprylylsilane, Disodium EDTA, PEG-8 Dimethicone, Aloe Barbadensis Leaf Juice Powder, Octyldodecanol, Retinyl Palmitate, Tocopheryl Acetate, Ascorbic Acid, Sodium Propoxyhydroxypropyl Thiosulfate Silica, Phenoxyethanol, Methylparaben, Propylparaben.

Principal Display Panel

Walgreens
Sunscreen
with ZINC OXIDE
SPF
70
GOES ON
CLEAR
GREASELESS
UVA/UVB
PROTECTION
DERMATOLOGIST TESTED
4 FL OZ (118 mL)

Uses

- helps prevent sunburn
- higher SPF gives more sunburn protection
- retains SPF after 80 minutes of activity in the water